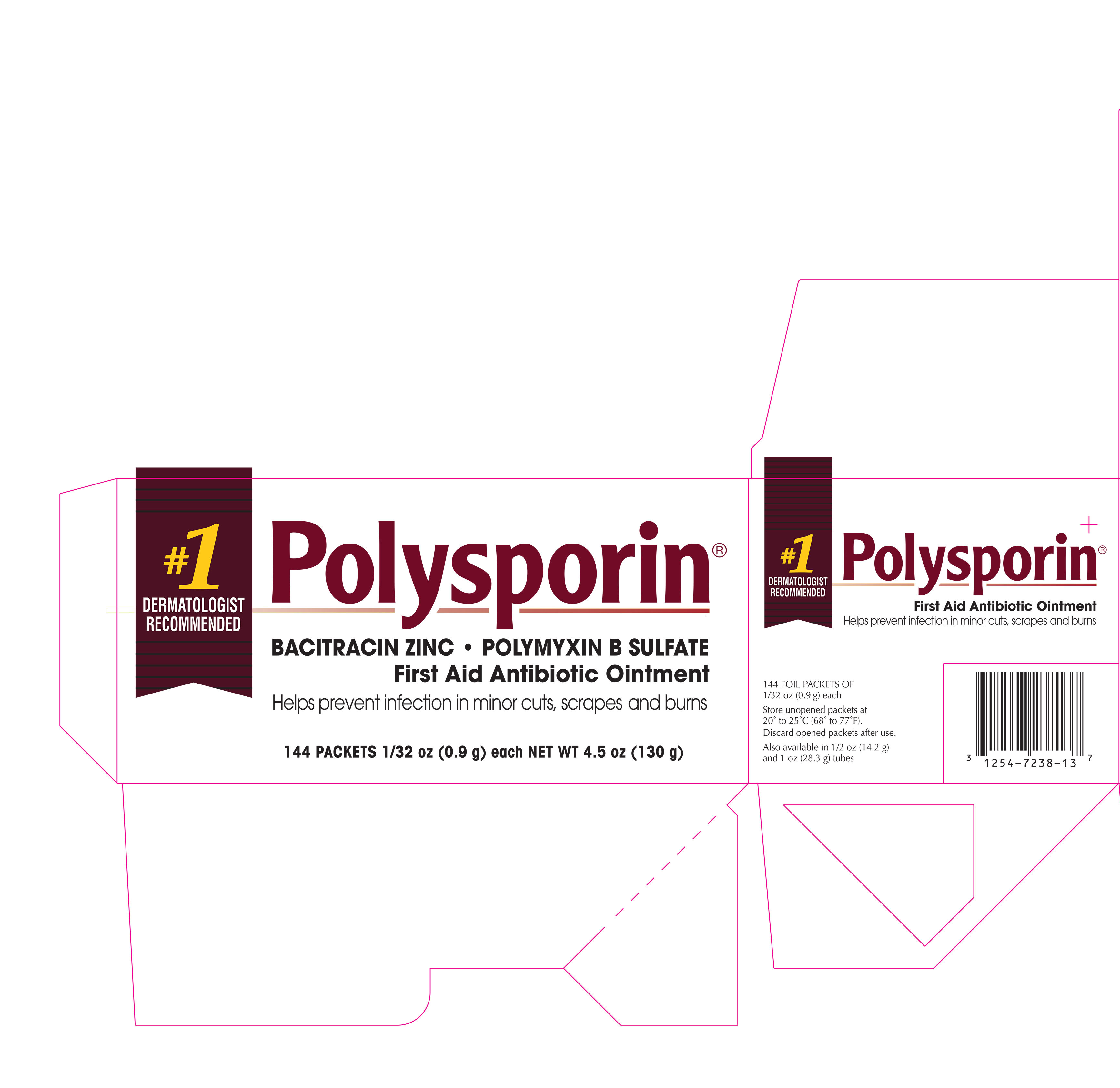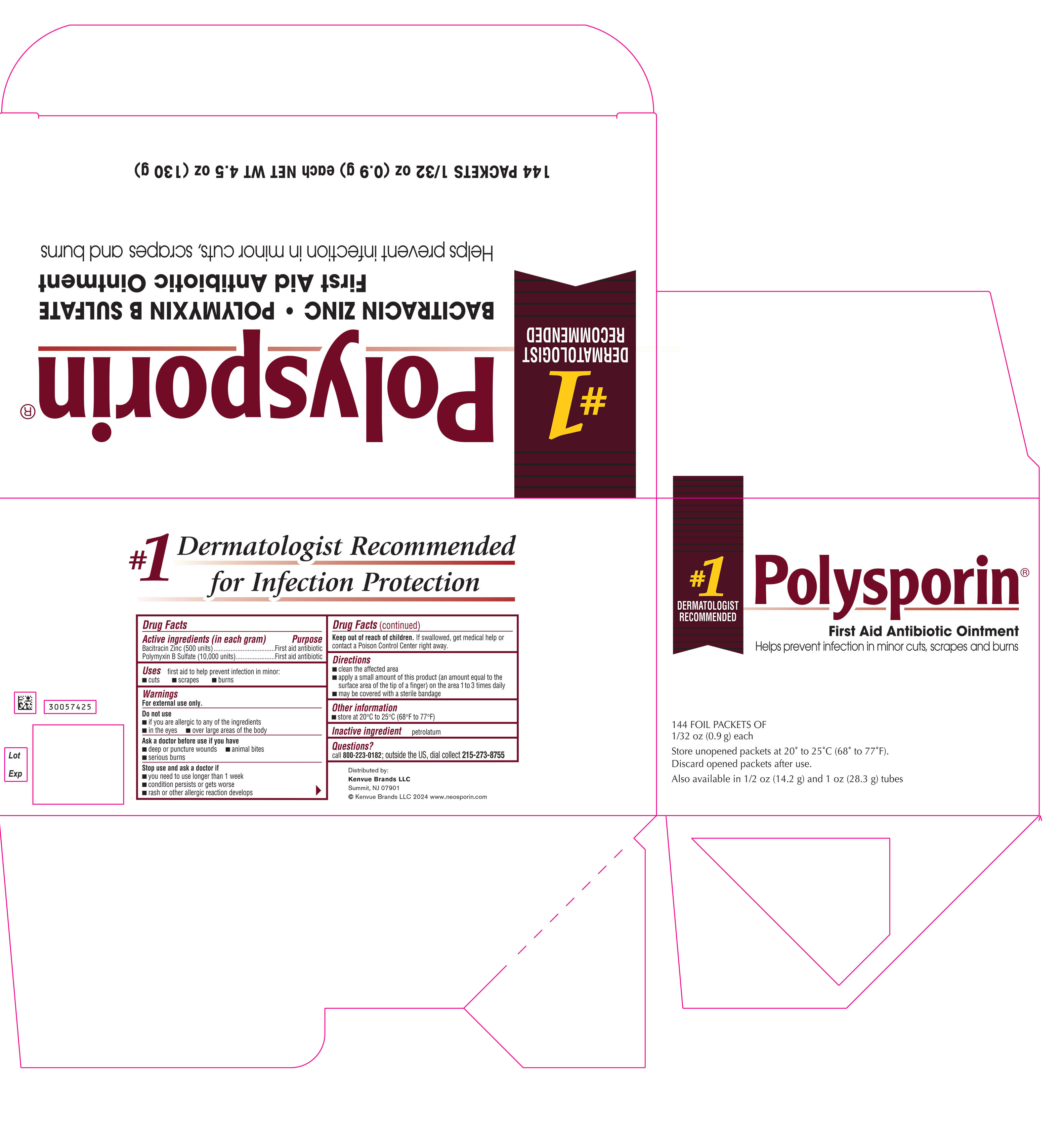 DRUG LABEL: Polysporin First Aid Antibiotic
NDC: 69968-0060 | Form: OINTMENT
Manufacturer: Kenvue Brands LLC
Category: otc | Type: HUMAN OTC DRUG LABEL
Date: 20241114

ACTIVE INGREDIENTS: BACITRACIN ZINC 500 [USP'U]/1 g; POLYMYXIN B SULFATE 10000 [USP'U]/1 g
INACTIVE INGREDIENTS: PETROLATUM

Polysporin® First Aid Antibiotic Ointment

Drug Facts

ACTIVE INGREDIENT

Active ingredients (in each gram) | Purpose
Bacitracin Zinc 500 units | First aid antibiotic
Polymyxin B Sulfate 10,000 units | First aid antibiotic

Use

first aid to help prevent infection in minor:

- cuts
- scrapes
- burns

Warnings

For external use only.

Do not use

- if you are allergic to any of the ingredients
- in the eyes
- over large areas of the body

Ask a doctor before use if you have

- deep or puncture wounds
- animal bites
- serious burns

Stop use and ask a doctor if

- you need to use longer than 1 week
- condition persists or gets worse
- rash or other allergic reaction develops

Keep out of reach of children. If swallowed, get medical help or contact a Poison Control Centre right away.

Directions

- clean the affected area
- apply a small amount of this product (an amount equal to the surface area of the tip of a finger) on the area 1 to 3 times daily
- may be covered with a sterile bandage

Other information

- store at 20° to 25°C (68° to 77°F)

Inactive ingredient

petrolatum

Questions?

call 800-223-0182 or 215-273-8755 (collect)

Distributed by:

Kenvue Brands LLC

Summit, NJ 07901

PRINCIPAL DISPLAY PANEL - 28.3 g Tube Carton

#1 DERMATOLOGIST
RECOMMENDED

Polysporin®

ANTIBIOTIC
OINTMENT

#1 Dermatologist
Recommended for
Infection Protection

Helps prevent
Infection in Minor Cuts,
Scrapes, and Burns

OINTMENT

FIRST AID ANTIBIOTIC OINTMENT
Bacitracin Zinc - Polymyxin B Sulfate

NET WT. 1 OZ (28.3 g)